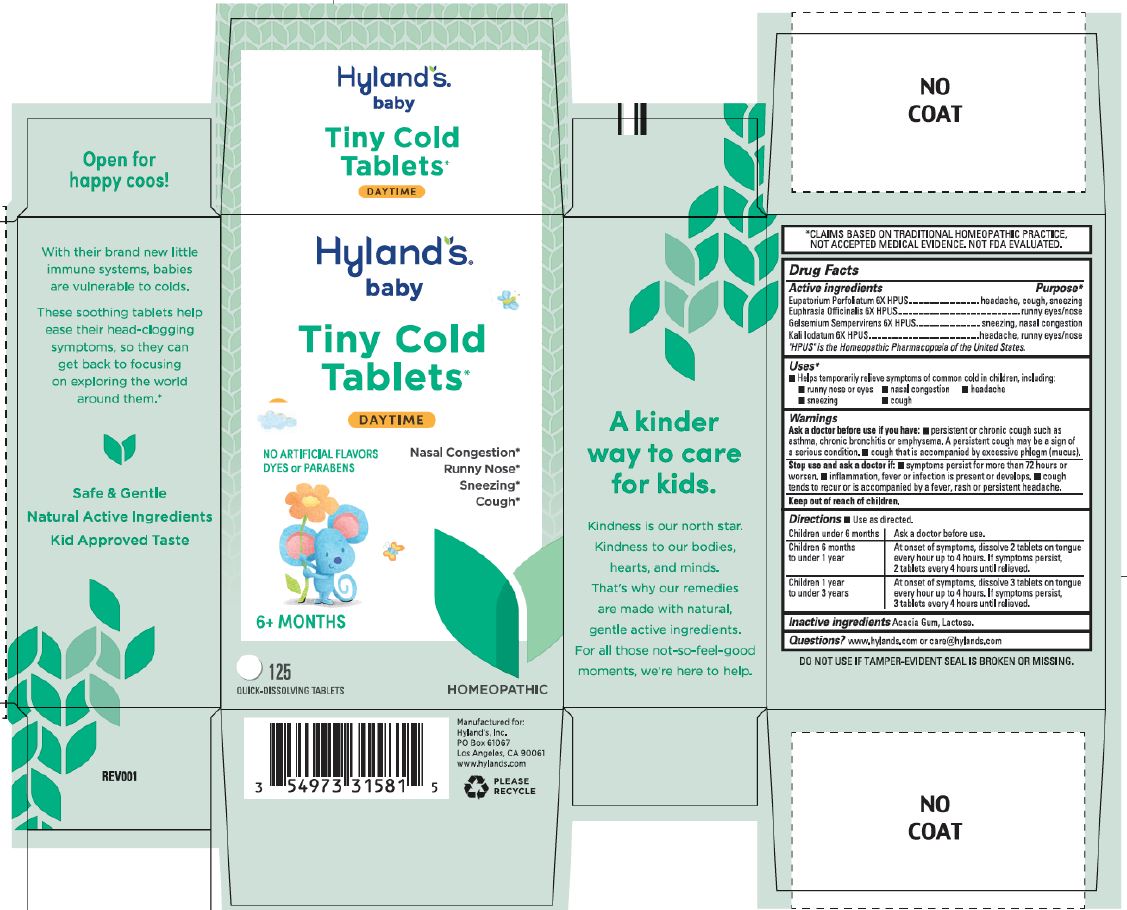 DRUG LABEL: Tiny Cold
NDC: 54973-3158 | Form: TABLET, SOLUBLE
Manufacturer: Hyland's Inc.
Category: homeopathic | Type: HUMAN OTC DRUG LABEL
Date: 20241121

ACTIVE INGREDIENTS: POTASSIUM IODIDE 6 [hp_X]/1 1; EUPATORIUM PERFOLIATUM FLOWERING TOP 6 [hp_X]/1 1; EUPHRASIA STRICTA 6 [hp_X]/1 1; GELSEMIUM SEMPERVIRENS ROOT 6 [hp_X]/1 1
INACTIVE INGREDIENTS: LACTOSE; ACACIA

Hyland's Naturals Baby Tiny Cold Tablets Daytime

PURPOSE

Relieves nasal congestion, runny nose, sneezing and cough

Drug Facts

Active ingredients | Purpose
Eupatorium Perfoliatum 6X HPUS | headache, cough, sneezing
Euphrasia Officinalis 6X HPUS | runny eyes/nose
Gelsemium Sempervirens 6X HPUS | sneezing, nasal congestion
Kali Iodatum 6X HPUS | headache, runny eyes/nose

"HPUS" indicates that the active ingredients are in the official Homeopathic

Pharmacopoeia of the United States.

Uses

■ Helps temporarily relieves symptoms of common cold in children, including:

■ runny nose or eyes ■ nasal congestion ■ headache

■ sneezing ■ cough

Warnings

Ask a doctor before use if you have:

■ persistent or chronic cough such as asthma, chronic bronchitis or emphysema. A persistent cough may be a sign of
a serious condition. ■ cough that is accompanied by excessive phlegm (mucus).

Stop use and ask a doctor if:

■ symptoms persist for more than 72 hours or worsen. ■ inflammation, fever or infection is present or develops. ■ cough
tends to recur or is accompanied by a fever, rash or persistent headache.

Directions

■ Use as directed.

Children under 6 months | Ask a doctor before use.
Children 6 months to under 1 year | At onset of symptoms, dissolve 2 tablets on tongue every hour up to 4 hours. If symptoms persist, 2 tablets every 4 hours until relieved.
Children 1 year to under 3 years | At onset of symptoms, dissolve 3 tablets on tongue every hour up to 4 hours. If symptoms persist, 3 tablets every 4 hours until relieved.

Inactive Ingredients

Acacia Gum, Lactose

Questions?

(800) 624-9659

Indications and Usage Dosage and Administration

 Temporarily relieves symptoms of common cold in children, including:

 runny nose or eyes  nasal congestion  headache  sneezing  cough

Directions

■ Use as directed.

Children under 6 months
Ask a doctor before use.
Children 6 months
to under 1 year
At onset of symptoms, dissolve 2 tablets on tongue every hour up to 4 hours. If symptoms persist,
2 tablets every 4 hours until relieved.
Children 1 year
to under 3 years
At onset of symptoms, dissolve 3 tablets on tongue every hour up to 4 hours. If symptoms persist,
3 tablets every 4 hours until relieved.

PRINCIPAL DISPLAY PANEL - Hyland's Baby Tiny Cold Tablets DAYTIME125 Tablets

Hyland's

•baby•

Tiny Cold

Tablets

DAYTIME